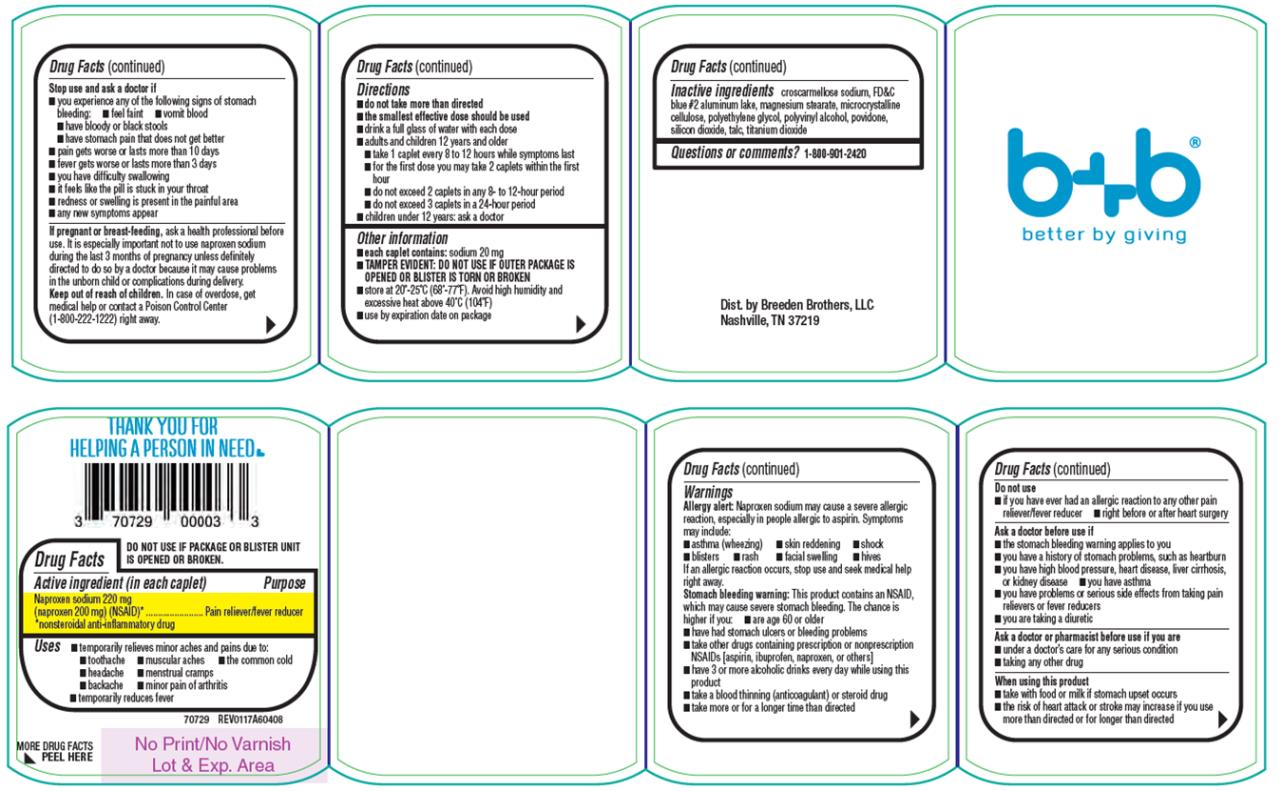 DRUG LABEL: Naproxen Sodium Caplets
NDC: 70729-003 | Form: TABLET
Manufacturer: Breeden Brothers, LLC
Category: otc | Type: HUMAN OTC DRUG LABEL
Date: 20170201

ACTIVE INGREDIENTS: NAPROXEN SODIUM 220 mg/1 1
INACTIVE INGREDIENTS: CROSCARMELLOSE SODIUM; FD&C BLUE NO. 2; MAGNESIUM STEARATE; CELLULOSE, MICROCRYSTALLINE; POLYETHYLENE GLYCOLS; POLYVINYL ALCOHOL, UNSPECIFIED; POVIDONE; SILICON DIOXIDE; TALC; TITANIUM DIOXIDE

Naproxen Sodium Caplets

Drug Facts

Active ingredient (in each caplet)

Naproxen sodium 220 mg (naproxen 200 mg) (NSAID)*
*nonsteroidal anti-inflammatory drug

Purpose

Pain reliever/fever reducer *nonsteroidal anti-inflammatory drug

Uses

_ temporarily relieves minor aches and pains due to:

_ toothache _ muscular aches _ the common cold

_ headache _ menstrual cramps

_ backache _ minor pain of arthritis

_ temporarily reduces fever

Drug Facts (continued)

Warnings

Allergy alert: Naproxen sodium may cause a severe allergic reaction, especially in people allergic to aspirin. Symptoms may include:

_ asthma (wheezing) _ skin reddening _ shock

_ blisters _ rash _ facial swelling _ hives

If an allergic reaction occurs, stop use and seek medical help right away.

Stomach bleeding warning: This product contains an NSAID, which may cause severe stomach bleeding. The chance is higher if you:

_ are age 60 or older

_ have had stomach ulcers or bleeding problems

_ take other drugs containing prescription or nonprescription NSAIDs [aspirin, ibuprofen, naproxen, or others]

_ have 3 or more alcoholic drinks every day while using this product

_ take a blood thinning (anticoagulant) or steroid drug

_ take more or for a longer time than directed

Drug Facts (continued)

Do not use

_ if you have ever had an allergic reaction to any other pain reliever/fever reducer

_ right before or after heart surgery

Ask a doctor before use if

_ the stomach bleeding warning applies to you

_ you have a history of stomach problems, such as heartburn

_ you have high blood pressure, heart disease, liver cirrhosis, or kidney disease _ you have asthma

_ you have problems or serious side effects from taking pain relievers or fever reducers

_ you are taking a diuretic

Ask a doctor or pharmacist before use if you are

_ under a doctor’s care for any serious condition

_ taking any other drug

When using this product

_ take with food or milk if stomach upset occurs

_ the risk of heart attack or stroke may increase if you use more than directed or for longer than directed

Drug Facts (continued)

Stop use and ask a doctor if

_ you experience any of the following signs of stomach bleeding:

_ feel faint _ vomit blood

_ have bloody or black stools

_ have stomach pain that does not get better

_ pain gets worse or lasts more than 10 days

_ fever gets worse or lasts more than 3 days

_ you have difficulty swallowing

_ it feels like the pill is stuck in your throat

_ redness or swelling is present in the painful area

_ any new symptoms appear

If pregnant or breast-feeding,

ask a health professional before use. It is especially important not to use naproxen sodium during the last 3 months of pregnancy unless definitely directed to do so by a doctor because it may cause problems in the unborn child or complications during delivery.

Keep out of reach of children.

In case of overdose, get medical help or contact a Poison Control Center (1-800-222-1222) right away.

Drug Facts (continued)

Directions

_ do not take more than directed

_ the smallest effective dose should be used

_ drink a full glass of water with each dose

_ adults and children 12 years and older take 1 caplet every 8 to 12 hours while symptoms last

_ for the first dose you may take 2 caplets within the first hour

_ do not exceed 2 caplets in any 8- to 12-hour period

_ do not exceed 3 caplets in a 24-hour period

_ children under 12 years: ask a doctor

Other information

_ each caplet contains: sodium 20 mg

_ TAMPER EVIDENT: DO NOT USE IF OUTER PACKAGE IS OPENED OR BLISTER IS TORN OR BROKEN

_ store at 20°-25°C (68°-77°F). Avoid high humidity and excessive heat above 40°C (104°F)

_ use by expiration date on package

Drug Facts (continued)

Inactive ingredients

croscarmellose sodium, FD&C blue #2 aluminum lake, magnesium stearate, microcrystalline cellulose, polyethylene glycol, polyvinyl alcohol, povidone, silicon dioxide, talc, titanium dioxide

Questions or comments?

1-800-901-2420

Dist. by Breeden Brothers, LLC
Nashville, TN 37219

PRINCIPAL DISPLAY PANEL

b+b
better by giving